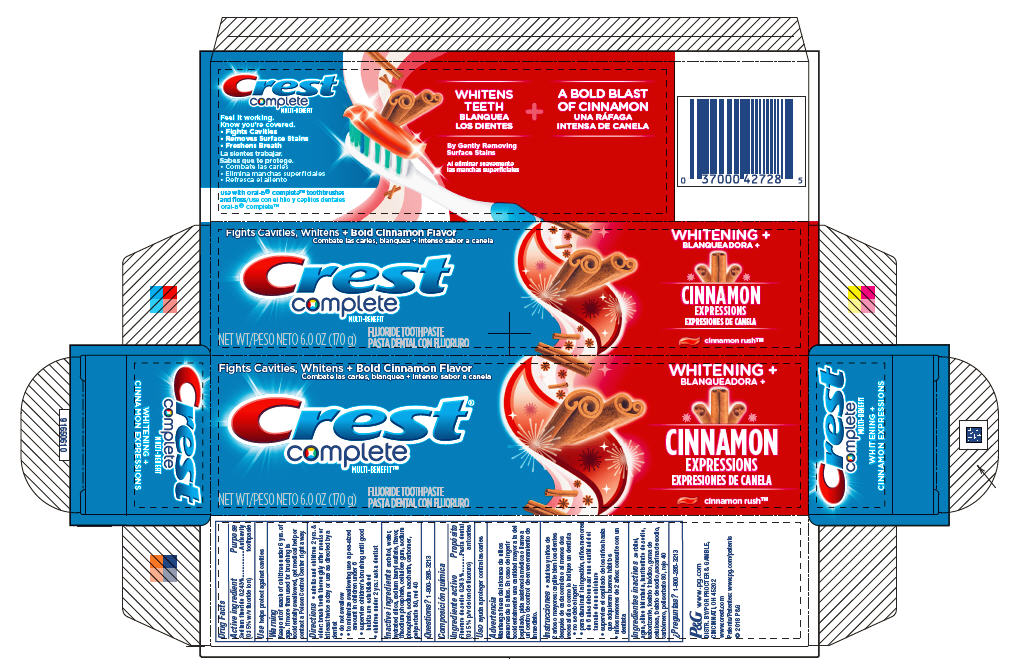 DRUG LABEL: Crest Complete Multi-Benefit
NDC: 37000-943 | Form: PASTE, DENTIFRICE
Manufacturer: The Procter & Gamble Manufacturing Company
Category: otc | Type: HUMAN OTC DRUG LABEL
Date: 20260108

ACTIVE INGREDIENTS: SODIUM FLUORIDE 1.5 mg/1 g
INACTIVE INGREDIENTS: CARBOXYPOLYMETHYLENE; POLYSORBATE 80; SORBITOL; SODIUM PHOSPHATE, TRIBASIC, ANHYDROUS; CARBOXYMETHYLCELLULOSE SODIUM; SODIUM PHOSPHATE, MONOBASIC, UNSPECIFIED FORM; FD&C RED NO. 40; WATER; HYDRATED SILICA; SODIUM LAURYL SULFATE; SACCHARIN SODIUM

Crest®
Complete
MULTI-BENEFIT™
WHITENING + CINNAMON EXPRESSIONS

Drug Facts

Active ingredient

Sodium fluoride 0.243%

(0.15% w/v fluoride ion)

Purpose

Anticavity toothpaste

Use

helps protect against cavities

Warnings

Keep out of reach of children under 6 yrs. of age. If more than used for brushing is accidentally swallowed, get medical help or contact a Poison Control Center right away.

Directions

- adults and children 2 yrs. & older: brush teeth thoroughly after meals or at least twice a day or use as directed by a dentist
  - do not swallow
  - to minimize swallowing use a pea-sized amount in children under 6
  - supervise children's brushing until good habits are established
- children under 2 yrs.: ask a dentist

Inactive ingredients

sorbitol, water, hydrated silica, sodium lauryl sulfate, flavor, trisodium phosphate, cellulose gum, sodium phosphate, sodium saccharin, carbomer, polysorbate 80, red 40

Questions?

1-800-285-3213

DISTR. BY PROCTER & GAMBLE,
CINCINNATI, OH 45202

PRINCIPAL DISPLAY PANEL - 170 g Tube Carton

Fights Cavities, Whitens + Bold Cinnamon Flavor

Crest®

complete

MULTI-BENEFIT™

NET WT 6.0 OZ (170g)

WHITENING +

CINNAMON EXPRESSIONS

cinnamon rush™